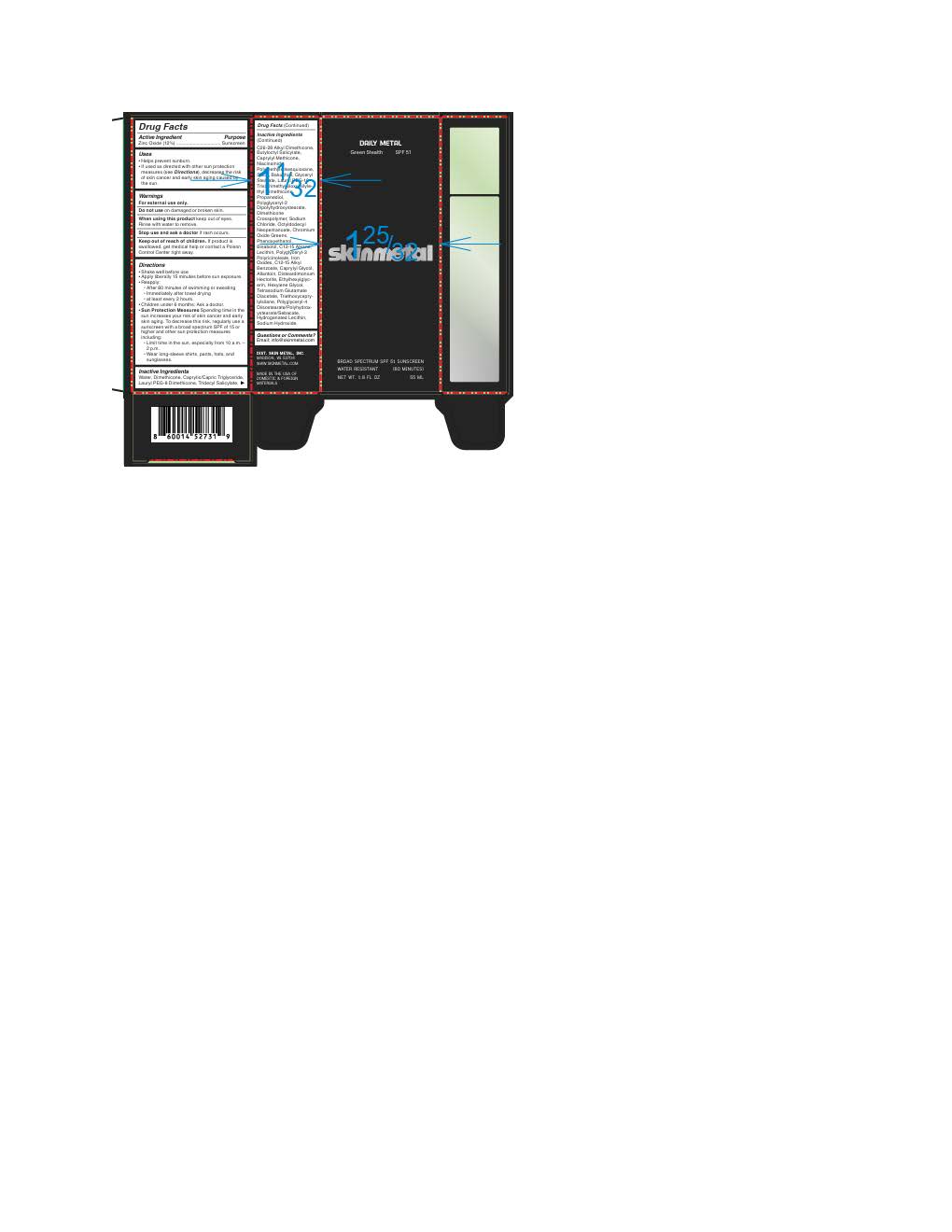 DRUG LABEL: Skin Metal Green Stealth
NDC: 87098-270 | Form: LOTION
Manufacturer: Skin Metal
Category: otc | Type: HUMAN OTC DRUG LABEL
Date: 20260109

ACTIVE INGREDIENTS: ZINC OXIDE 132 mg/1 mL
INACTIVE INGREDIENTS: BAKUCHIOL; CI 77288; TRIETHOXYCAPRYLYLSILANE; SODIUM HYDROXIDE; C13-15 ALKANE; GLYCERYL STEARATE; LAURYL PEG-8 DIMETHICONE (300 CPS); OCTYLDODECYL NEOPENTANOATE; CAPRYLYL METHICONE; HYDROGENATED SOYBEAN LECITHIN; POLYGLYCERYL-4 DIISOSTEARATE/POLYHYDROXYSTEARATE/SEBACATE; POLYMETHYLSILSESQUIOXANE (4.5 MICRONS); CAPRYLYL GLYCOL; ALLANTOIN; .ALPHA.-BISABOLOL, (+)-; BUTYLOCTYL SALICYLATE; NIACINAMIDE; WATER; ETHYLHEXYLGLYCERIN; HEXYLENE GLYCOL; PROPANEDIOL; TETRASODIUM GLUTAMATE DIACETATE; SODIUM CHLORIDE; PHENOXYETHANOL; DIMETHICONE; ALKYL (C12-15) BENZOATE; CAPRYLIC/CAPRIC TRIGLYCERIDE; DIMETHICONE CROSSPOLYMER; SILICON DIOXIDE; CI 77492; DISTEARDIMONIUM HECTORITE; TRIDECYL SALICYLATE

Skin Metal Green Stealth